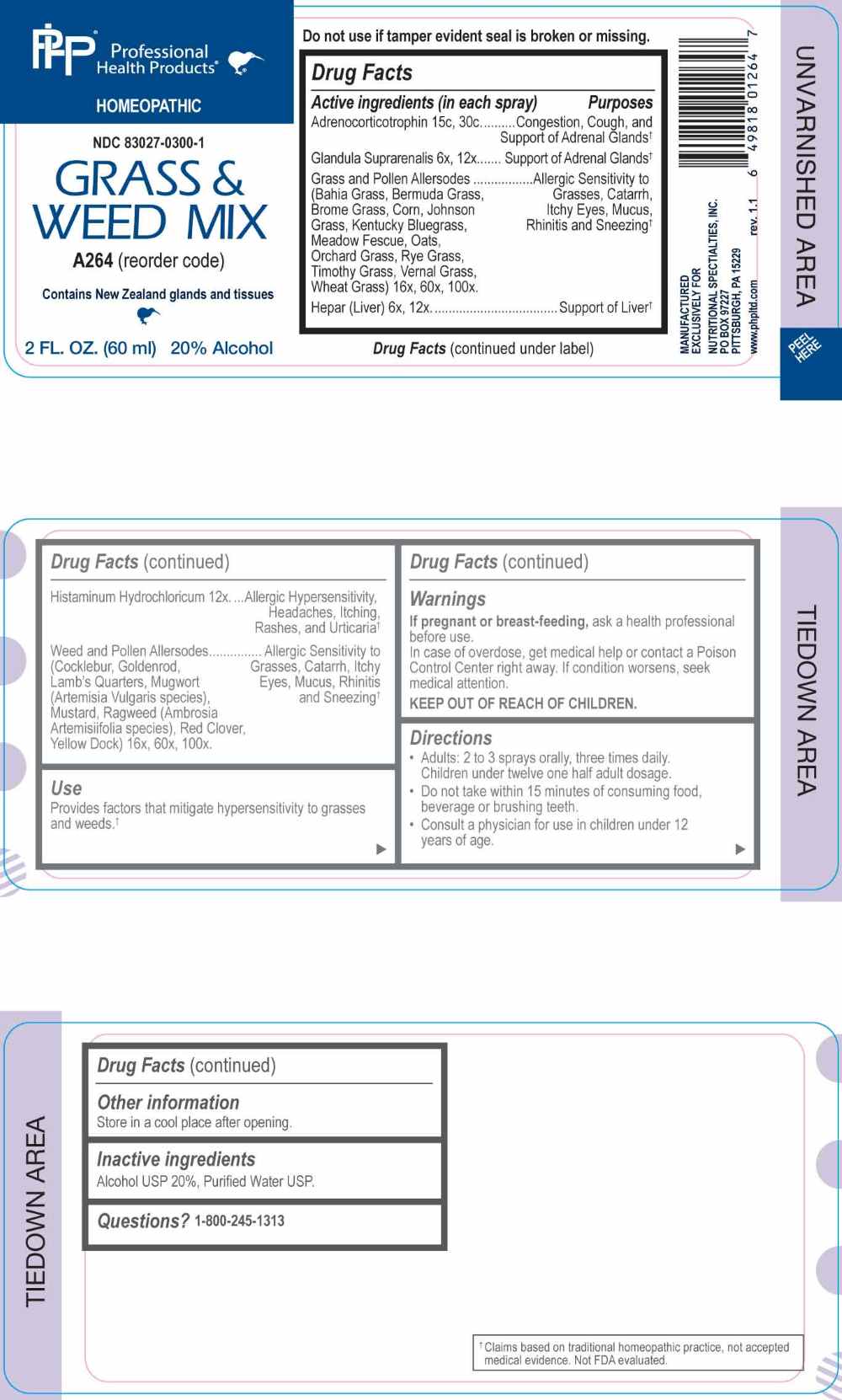 DRUG LABEL: Grass and Weed Mix
NDC: 83027-0300 | Form: SPRAY
Manufacturer: Nutritional Specialties, Inc.
Category: homeopathic | Type: HUMAN OTC DRUG LABEL
Date: 20260220

ACTIVE INGREDIENTS: BOS TAURUS ADRENAL GLAND 6 [hp_X]/1 mL; BEEF LIVER 6 [hp_X]/1 mL; HISTAMINE DIHYDROCHLORIDE 12 [hp_X]/1 mL; PASPALUM NOTATUM POLLEN 16 [hp_X]/1 mL; CYNODON DACTYLON WHOLE 16 [hp_X]/1 mL; BROMUS INERMIS POLLEN 16 [hp_X]/1 mL; ZEA MAYS POLLEN 16 [hp_X]/1 mL; SORGHUM HALEPENSE POLLEN 16 [hp_X]/1 mL; POA PRATENSIS TOP 16 [hp_X]/1 mL; LOLIUM PRATENSE POLLEN 16 [hp_X]/1 mL; AVENA SATIVA POLLEN 16 [hp_X]/1 mL; DACTYLIS GLOMERATA TOP 16 [hp_X]/1 mL; LOLIUM PERENNE TOP 16 [hp_X]/1 mL; PHLEUM PRATENSE TOP 16 [hp_X]/1 mL; ANTHOXANTHUM ODORATUM POLLEN 16 [hp_X]/1 mL; TRITICUM AESTIVUM POLLEN 16 [hp_X]/1 mL; CORTICOTROPIN 15 [hp_C]/1 mL; XANTHIUM STRUMARIUM POLLEN 16 [hp_X]/1 mL; SOLIDAGO CANADENSIS POLLEN 16 [hp_X]/1 mL; CHENOPODIUM ALBUM POLLEN 16 [hp_X]/1 mL; ARTEMISIA VULGARIS POLLEN 16 [hp_X]/1 mL; BRASSICA RAPA SUBSP. OLEIFERA POLLEN 16 [hp_X]/1 mL; AMBROSIA ARTEMISIIFOLIA POLLEN 16 [hp_X]/1 mL; TRIFOLIUM PRATENSE POLLEN 16 [hp_X]/1 mL; RUMEX CRISPUS POLLEN 16 [hp_X]/1 mL
INACTIVE INGREDIENTS: WATER; ALCOHOL

DRUG FACTS:

ACTIVE INGREDIENTS:

(in each spray) Adrenocorticotrophin 15C, 30C, Glandula Suprarenalis 6X, 12X, Bahia Grass 16X, 60X, 100X, Bermuda Grass 16X, 60X, 100X, Brome Grass 16X, 60X, 100X, Corn 16X, 60X, 100X, Johnson Grass 16X, 60X, 100X, Kentucky Bluegrass 16X, 60X, 100X, Meadow Fescue 16X, 60X, 100X, Oats 16X, 60X, 100X, Orchard Grass 16X, 60X, 100X, Rye Grass 16X, 60X, 100X, Timothy Grass 16X, 60X, 100X, Vernal Grass 16X, 60X, 100X, Wheat Grass 16X, 60X, 100X, Hepar (Liver) 6X, 12X, Histaminum Hydrochloricum 12X, Cocklebur 16X, 60X, 100X, Goldenrod 16X, 60X, 100X, Lambs Quarters 16X, 60X, 100X, Mugwort (Artemisia Vulgaris species) 16X, 60X, 100X, Mustard 16X, 60X, 100X, Ragweed (Ambrosia Artemisiifolia species) 16X, 60X, 100X, Red Clover 16X, 60X, 100X, Yellow Dock 16X, 60X, 100X.

PURPOSE:

Adrenocorticotrophin – Congestion, Cough, and Support of Adrenal Glands,† Glandula Suprarenalis – Support of Adrenal Glands,† Bahia Grass – Allergic Sensitivity to Grasses, Catarrh, Itchy Eyes, Mucus, Rhinitis and Sneezing,† Bermuda Grass - Allergic Sensitivity to Grasses, Catarrh, Itchy Eyes, Mucus, Rhinitis and Sneezing,† Brome Grass - Allergic Sensitivity to Grasses, Catarrh, Itchy Eyes, Mucus, Rhinitis and Sneezing,† Corn - Allergic Sensitivity to Grasses, Catarrh, Itchy Eyes, Mucus, Rhinitis and Sneezing,† Johnson Grass - Allergic Sensitivity to Grasses, Catarrh, Itchy Eyes, Mucus, Rhinitis and Sneezing,† Kentucky Bluegrass - Allergic Sensitivity to Grasses, Catarrh, Itchy Eyes, Mucus, Rhinitis and Sneezing,† Meadow Fescue - Allergic Sensitivity to Grasses, Catarrh, Itchy Eyes, Mucus, Rhinitis and Sneezing,† Oats - Allergic Sensitivity to Grasses, Catarrh, Itchy Eyes, Mucus, Rhinitis and Sneezing,† Orchard Grass - Allergic Sensitivity to Grasses, Catarrh, Itchy Eyes, Mucus, Rhinitis and Sneezing,† Rye Grass - Allergic Sensitivity to Grasses, Catarrh, Itchy Eyes, Mucus, Rhinitis and Sneezing,† Timothy Grass - Allergic Sensitivity to Grasses, Catarrh, Itchy Eyes, Mucus, Rhinitis and Sneezing,† Vernal Grass - Allergic Sensitivity to Grasses, Catarrh, Itchy Eyes, Mucus, Rhinitis and Sneezing,† Wheat Grass - Allergic Sensitivity to Grasses, Catarrh, Itchy Eyes, Mucus, Rhinitis and Sneezing,† Hepar (Liver) – Support of Liver,† Histaminum Hydrochloricum – Allergic Hypersensitivity, Headaches, Itching, Rashes, and Urticaria,† Cocklebur – Allergic Sensitivity to Grasses, Catarrh, Itchy Eyes, Mucus, Rhinitis and Sneezing,† Goldenrod - Allergic Sensitivity to Grasses, Catarrh, Itchy Eyes, Mucus, Rhinitis and Sneezing,† Lambs Quarters - Allergic Sensitivity to Grasses, Catarrh, Itchy Eyes, Mucus, Rhinitis and Sneezing,† Mugwort (Artemisia Vulgaris species - Allergic Sensitivity to Grasses, Catarrh, Itchy Eyes, Mucus, Rhinitis and Sneezing,† Mustard - Allergic Sensitivity to Grasses, Catarrh, Itchy Eyes, Mucus, Rhinitis and Sneezing,† Ragweed (Ambrosia Artemisiifolia species) - Allergic Sensitivity to Grasses, Catarrh, Itchy Eyes, Mucus, Rhinitis and Sneezing,† Red Clover - Allergic Sensitivity to Grasses, Catarrh, Itchy Eyes, Mucus, Rhinitis and Sneezing,† Yellow Dock - Allergic Sensitivity to Grasses, Catarrh, Itchy Eyes, Mucus, Rhinitis and Sneezing†

†Claims based on traditional homeopathic practice, not accepted medical evidence. Not FDA evaluated.

USES:

Provides factors that mitigate hypersensitivity to grasses.†

†Claims based on traditional homeopathic practice, not accepted medical evidence. Not FDA evaluated.

WARNINGS:

If pregnant or breast-feeding, ask a health professional before use.

In case of overdose, get medical help or contact a Poison Control Center right away.

If condition worsens, seek medical attention.

KEEP OUT OF REACH OF CHILDREN

Do not use if tamper evident seal is broken or missing.

Store in a cool place after opening

KEEP OUT OF REACH OF CHILDREN:

In case of overdose, get medical help or contact a Poison Control Center right away.

DIRECTIONS:

• Adults: 2 to 3 sprays orally, three times daily. Children under twelve one half adult dosage.

• Do not take within 15 minutes of consuming food, beverage or brushing teeth.

Consult a physician for use in children under 12 years of age.

INACTIVE INGREDIENTS:

Alcohol USP 20%, Purified Water USP.

QUESTIONS:

MANUFACTURED EXCLUSIVELY FOR

NUTRITIONAL SPECIALTIES, INC.

PO BOX 97227

PITTSBURG, PA 15229

www.phpltd.com

1-800-245-1313

PACKAGE LABEL DISPLAY:

Professional

Health Products

HOMEOPATHIC

NDC 83027-0300-1

GRASS & WEED MIX

2 FL. OZ (60 ml)